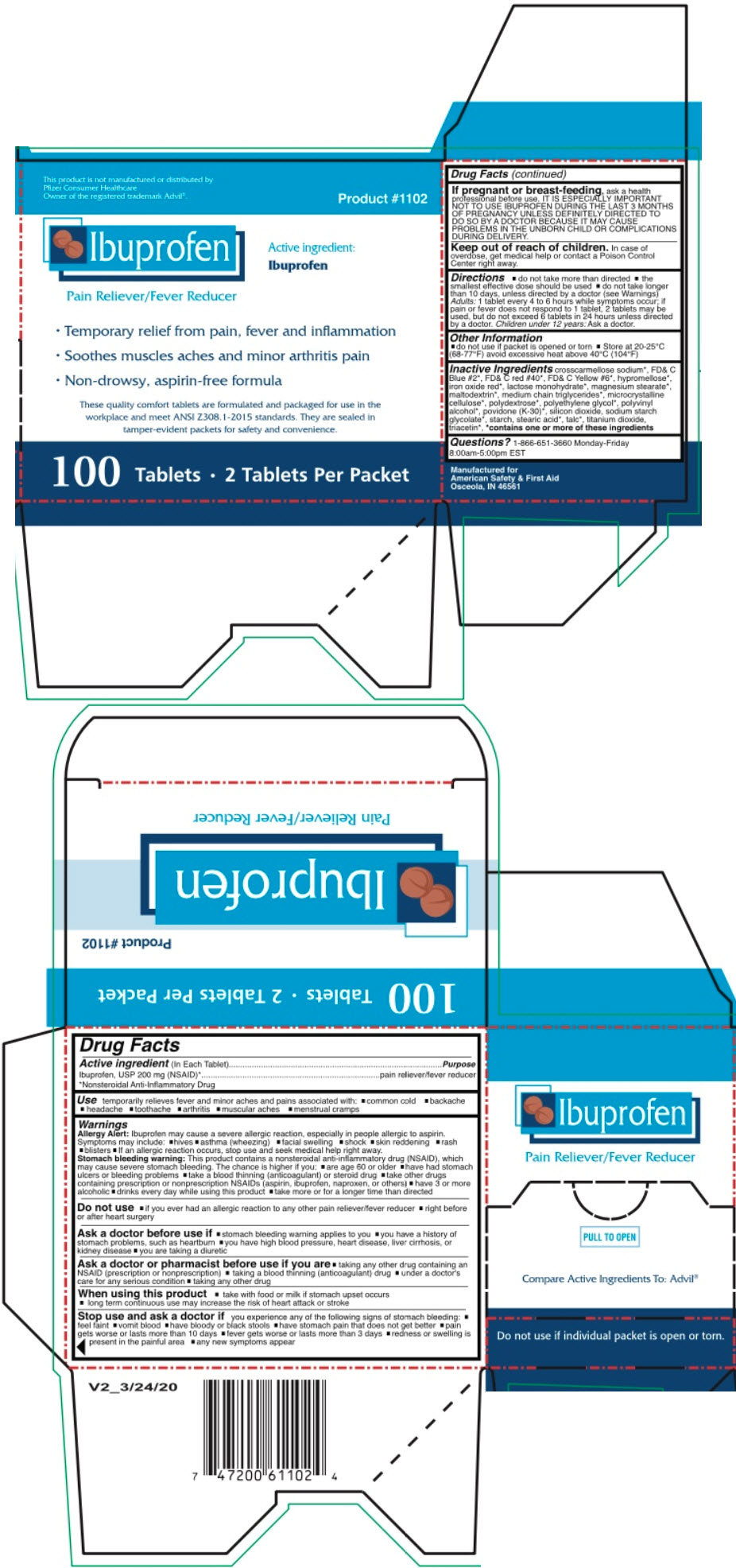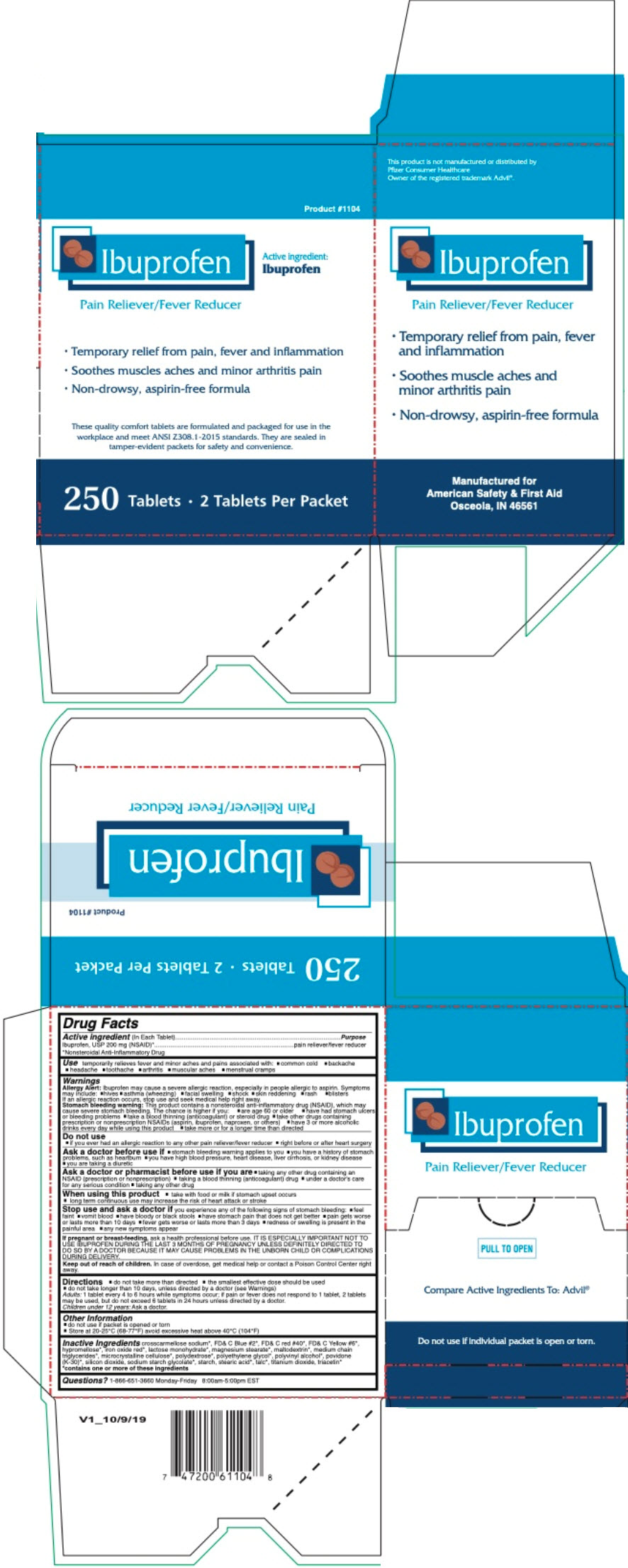 DRUG LABEL: IBUPROFEN 100
NDC: 73598-1102 | Form: TABLET, COATED
Manufacturer: JHK Inc dba American Safety & First Aid
Category: otc | Type: HUMAN OTC DRUG LABEL
Date: 20240425

ACTIVE INGREDIENTS: IBUPROFEN 200 mg/1 1
INACTIVE INGREDIENTS: CROSCARMELLOSE SODIUM; FD&C BLUE NO. 2; FD&C RED NO. 40; FD&C YELLOW NO. 6; HYPROMELLOSE, UNSPECIFIED; FERRIC OXIDE RED; LACTOSE MONOHYDRATE; MAGNESIUM STEARATE; MALTODEXTRIN; MEDIUM-CHAIN TRIGLYCERIDES; MICROCRYSTALLINE CELLULOSE; POLYDEXTROSE; POLYETHYLENE GLYCOL, UNSPECIFIED; POLYVINYL ALCOHOL, UNSPECIFIED; POVIDONE K30; SILICON DIOXIDE; SODIUM STARCH GLYCOLATE TYPE A; STARCH, CORN; STEARIC ACID; TALC; TITANIUM DIOXIDE; TRIACETIN

IBUPROFEN

Drug Facts

Active ingredient (In Each Tablets)

Ibuprofen, USP 200 mg (NSAID)

*Nonsteroidal Anti-Inflammatory Drug

Purpose

pain reliever/fever reducer

Use

temporarily relieves fever and minor aches and pains associated with:

- common cold
- backache
- headache
- toothache
- arthritis
- muscular aches
- menstrual cramps

Warnings

Allergy Alert

Ibuprofen may cause a severe allergic reaction, especially in people allergic to aspirin. Symptoms may include:

- hives
- asthma (wheezing)
- facial swelling
- shock
- skin reddening
- rash
- blisters
- If an allergic reaction occurs, stop use and seek medical help right away.

Stomach bleeding warning

This product contains a nonsteroidal anti-inflammatory drug (NSAID), which may cause severe stomach bleeding. The chance is higher if you:

- are age 60 or older
- have had stomach ulcers or bleeding problems
- take a blood thinning (anticoagulant) or steroid drug
- take other drugs containing prescription or nonprescription NSAIDs (aspirin, ibuprofen, naproxen, or others)
- have 3 or more alcoholic
- drinks every day while using this product
- take more or for a longer time than directed

Do not use

- if you ever had an allergic reaction to any other pain reliever/fever reducer
- right before or after heart surgery

Ask a doctor before use if

- stomach bleeding warning applies to you
- you have a history of stomach problems, such as heartburn
- you have high blood pressure, heart disease, liver cirrhosis, or kidney disease
- you are taking a diuretic

Ask a doctor or pharmacist before use if you are

- taking any other drug containing an NSAID (prescription or nonprescription)
- taking a blood thinning (anticoagulant) drug
- under a doctor's care for any serious condition
- taking any other drug

When using this product

- take with food or milk if stomach upset occurs
- long term continuous use may increase the risk of heart attack or stroke

Stop use and ask a doctor if you experience any of the following signs of stomach bleeding:

- feel faint
- vomit blood
- have bloody or black stools
- have stomach pain that does not get better
- pain gets worse or lasts more than 10 days
- fever gets worse or lasts more than 3 days
- redness or swelling is present in the painful area
- any new symptoms appear

PREGNANCY OR BREAST FEEDING

If pregnant or breast-feeding, ask a health professional before use. IT IS ESPECIALLY IMPORTANT NOT TO USE IBUPROFEN DURING THE LAST 3 MONTHS OF PREGNANCY UNLESS DEFINITELY DIRECTED TO DO SO BY A DOCTOR BECAUSE IT MAY CAUSE PROBLEMS IN THE UNBORN CHILD OR COMPLICATIONS DURING DELIVERY.

Keep out of reach of children. In case of overdose, get medical help or contact a Poison Control Center right away.

Directions

- do not take more than directed
- the smallest effective dose should be used
- do not take longer than 10 days, unless directed by a doctor (see Warnings)

Adults: 1 tablet every 4 to 6 hours while symptoms occur; if pain or fever does not respond to 1 tablet, 2 tablets may be used, but do not exceed 6 tablets in 24 hours unless directed by a doctor.

Children under 12 years: Ask a doctor.

Other Information

- do not use if packet is opened or torn
- Store at 20-25°C (68-77°F) avoid excessive heat above 40°C (104°F)

Inactive Ingredients

crosscarmellose sodium [contains one or more of these ingredients] , FD& C Blue #2, FD& C red #40, FD& C Yellow #6, hypromellose, iron oxide red, lactose monohydrate, magnesium stearate, maltodextrin, medium chain triglycerides, microcrystalline cellulose, polydextrose, polyethylene glycol, polyvinyl alcohol, povidone (K-30), silicon dioxide, sodium starch glycolate, starch, stearic acid, talc, titanium dioxide, triacetin,

Questions?

1-866-651-3660 Monday-Friday

8:00am-5:00pm EST

PRINCIPAL DISPLAY PANEL - 100 Tablet Packet Box

This product is not manufactured or distributed by
Pfizer Consumer Healthcare
Owner of the registered trademark Advil®.

Product #1102

Ibuprofen

Pain Reliever/Fever Reducer

Active ingredient:
Ibuprofen

- Temporary relief from pain, fever and inflammation
- Soothes muscles aches and minor arthritis pain
- Non-drowsy, aspirin-free formula

These quality comfort tablets are formulated and packaged for use in the
workplace and meet ANSI Z308.1-2015 standards. They are sealed in
tamper-evident packets for safety and convenience.

100 Tablets • 2 Tablets Per Packet

PRINCIPAL DISPLAY PANEL - 250 Tablet Packet Box

Product #1104

Ibuprofen

Pain Reliever/Fever Reducer

Active ingredient:
Ibuprofen

- Temporary relief from pain, fever and inflammation
- Soothes muscles aches and minor arthritis pain
- Non-drowsy, aspirin-free formula

These quality comfort tablets are formulated and packaged for use in the
workplace and meet ANSI Z308.1-2015 standards. They are sealed in
tamper-evident packets for safety and convenience.

250 Tablets • 2 Tablets Per Packet